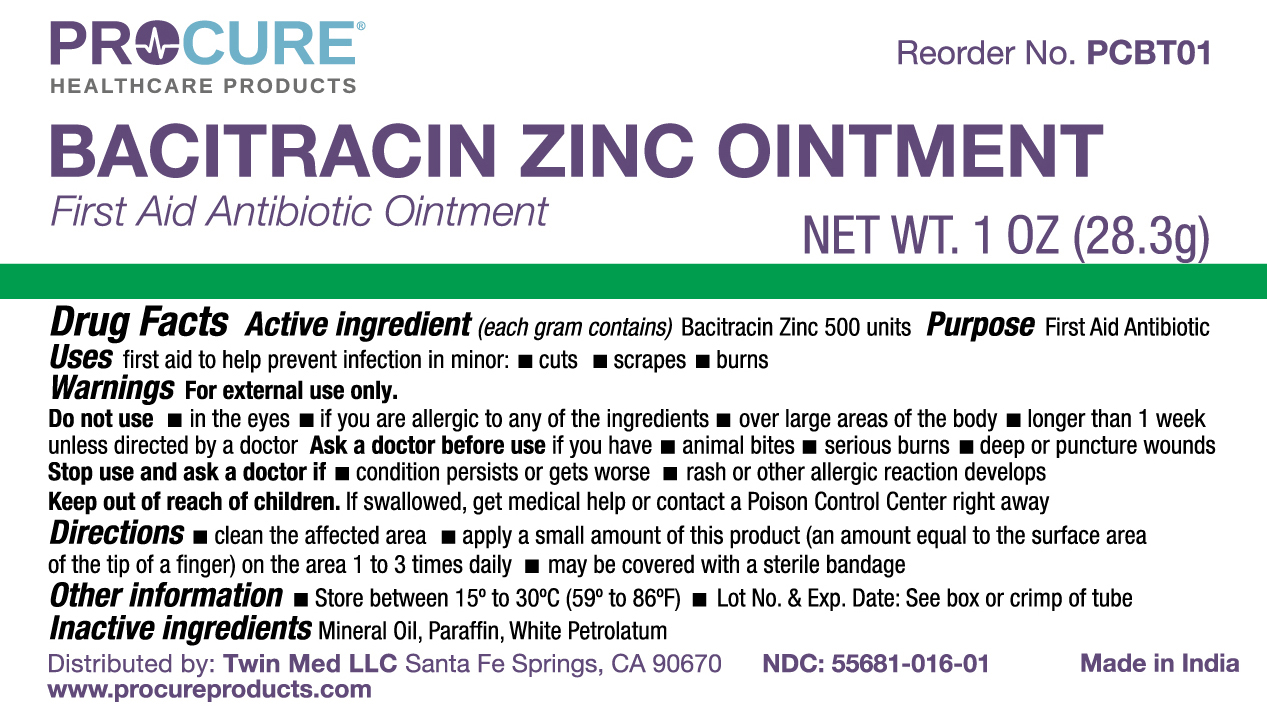 DRUG LABEL: ProCure Bacitracin Zinc
NDC: 55681-016 | Form: OINTMENT
Manufacturer: Twin Med LLC
Category: otc | Type: HUMAN OTC DRUG LABEL
Date: 20250605

ACTIVE INGREDIENTS: BACITRACIN ZINC 500 [iU]/1 g
INACTIVE INGREDIENTS: PARAFFIN; WHITE PETROLATUM; MINERAL OIL

Active Ingredient

Bacitracin Zinc 500 units

Purpose

First Aid Antibiotic

Uses

First aid to help prevent infection in minor: cuts, scrapes, burns

Warnings

For External Use Only

Do Not Use

- In the eyes
- if you are allergic to any of the ingredients
- over large areas of the body
- longer than 1 week unles directed by a doctor

Ask a doctor before use if you have:

- animal bites
- serious burns
- deep or puncture wounds

Stop use and ask a doctor if

- condition persists or gets worse
- rash or other allergic reaction develops

Keep out of reach of children. If swallowed, get medical help or contact a Poison Control Center right away

Directions

- clean the affected area
- apply a small amount of this product (an amount equal to the surface area of the tip of a finger) on the area 1 to 3 times daily
- may be covered with a sterile bandage

Inactive Ingredients

Inactive Ingredients: Mineral Oil, Paraffin, White Petrolatum